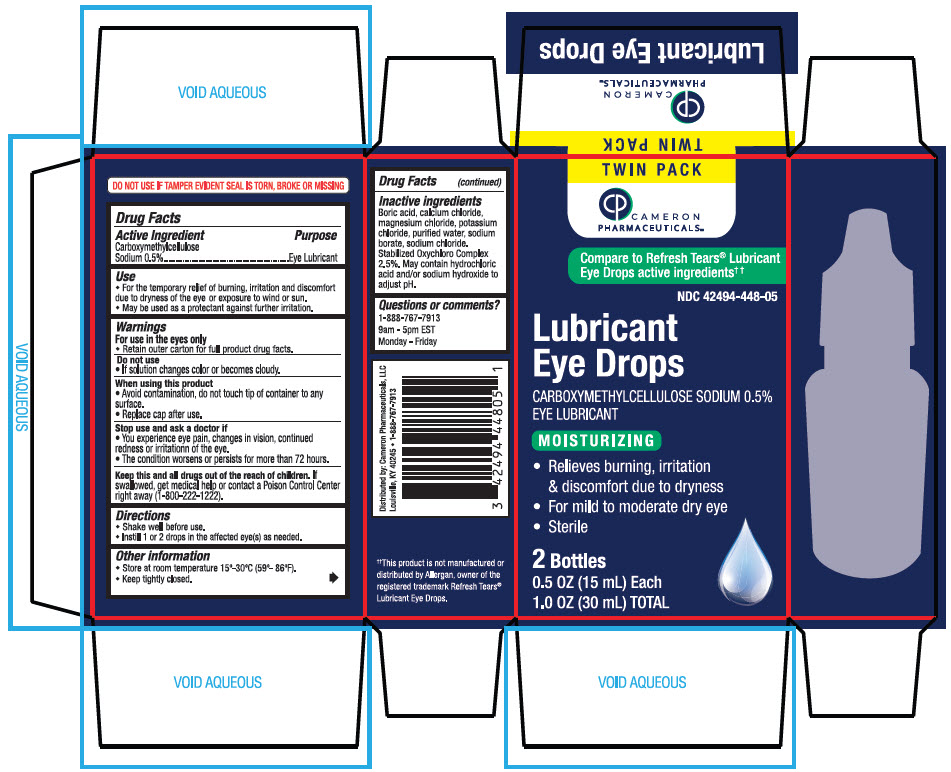 DRUG LABEL: CARBOXYMETHYLCELLULOSE SODIUM EYE LUBRICANT
NDC: 42494-448 | Form: SOLUTION/ DROPS
Manufacturer: Cameron Pharmaceuticals
Category: otc | Type: HUMAN OTC DRUG LABEL
Date: 20241107

ACTIVE INGREDIENTS: CARBOXYMETHYLCELLULOSE SODIUM, UNSPECIFIED 5 mg/1 mL
INACTIVE INGREDIENTS: CALCIUM CHLORIDE; MAGNESIUM CHLORIDE; POTASSIUM CHLORIDE; WATER; SODIUM CHLORIDE; SODIUM LACTATE; HYDROCHLORIC ACID; SODIUM HYDROXIDE

CARBOXYMETHYLCELLULOSE SODIUM 0.5% EYE LUBRICANT

Drug Facts

Active Ingredient

Carboxymethylcellulose Sodium 0.5%

Purpose

Eye Lubricant

Use

- For the temporary relief of burning, irritation and discomfort due to dryness of the eye or exposure to wind or sun.
- May be used as a protectant against further irritation.

Warnings

For use in the eyes only

- Retain outer carton for full product drug facts.

Do not use

- If solution changes color or becomes cloudy.

When using this product

- Avoid contamination, do not touch tip of container to any surface.
- Replace cap after use.

Stop use and ask a doctor if

- You experience eye pain, changes in vision, continued redness or irritationn of the eye.
- The condition worsens or persists for more than 72 hours.

KEEP OUT OF REACH OF CHILDREN

Keep this and all drugs out of the reach of children. If swallowed, get medical help or contact a Poison Control Center right away (1-800-222-1222).

Directions

- Shake well before use.
- Instill 1 or 2 drops in the affected eye(s) as needed.

Other information

- Store at room temperature 15°-30°C (59°- 86°F).
- Keep tightly closed.

Inactive ingredients

Boric acid, calcium chloride, magnesium chloride, potassium chloride, purified water, sodium borate, sodium chloride. Stabilized Oxychloro Complex 2.5%. May contain hydrochloric acid and/or sodium hydroxide to adjust pH.

Questions or comments?

1-888-767-7913
9am - 5pm EST
Monday - Friday

Distributed by: Cameron Pharmaceuticals, LLC
Louisville, KY 40245

PRINCIPAL DISPLAY PANEL - 2 Bottle Carton

TWIN PACK

CAMERON
PHARMACEUTICALS™

Compare to Refresh Tears® Lubricant
Eye Drops active ingredients† †

NDC 42494-448-05

Lubricant
Eye Drops

CARBOXYMETHYLCELLULOSE SODIUM 0.5%
EYE LUBRICANT

MOISTURIZING

- Relieves burning, irritation
  & discomfort due to dryness
- For mild to moderate dry eye
- Sterile

2 Bottles

0.5 OZ (15 mL) Each

1.0 OZ (30 mL) TOTAL